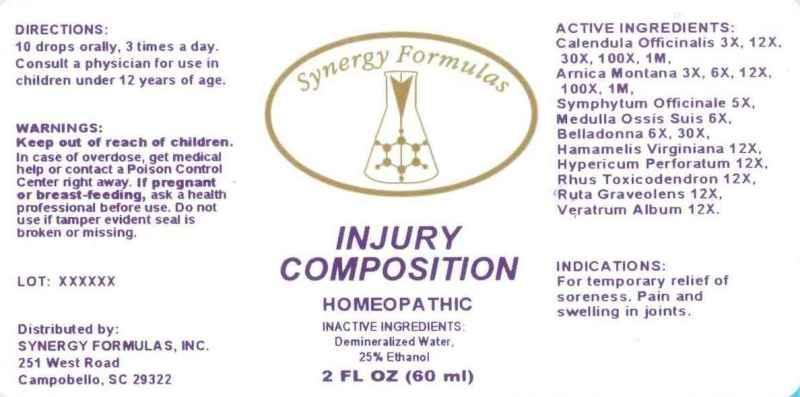 DRUG LABEL: INJURY COMPOSITION
NDC: 43772-0028 | Form: LIQUID
Manufacturer: Synergy Formulas, Inc.
Category: homeopathic | Type: HUMAN OTC DRUG LABEL
Date: 20150116

ACTIVE INGREDIENTS: CALENDULA OFFICINALIS FLOWERING TOP 3 [hp_X]/1 mL; ARNICA MONTANA 3 [hp_X]/1 mL; COMFREY ROOT 5 [hp_X]/1 mL; SUS SCROFA BONE MARROW 6 [hp_X]/1 mL; ATROPA BELLADONNA 6 [hp_X]/1 mL; HAMAMELIS VIRGINIANA ROOT BARK/STEM BARK 12 [hp_X]/1 mL; HYPERICUM PERFORATUM 12 [hp_X]/1 mL; TOXICODENDRON PUBESCENS LEAF 12 [hp_X]/1 mL; RUTA GRAVEOLENS FLOWERING TOP 12 [hp_X]/1 mL; VERATRUM ALBUM ROOT 12 [hp_X]/1 mL
INACTIVE INGREDIENTS: WATER; ALCOHOL

DRUG FACTS:

ACTIVE INGREDIENTS:

CALENDULA OFFICINALIS 3X, 12X, 30X, 100X, 1M, ARNICA MONTANA 3X, 6X, 12X, 100X, 1M, SYMPHYTUM OFFICINALE 5X, MEDULLA OSSIS SUIS 6X, BELLADONNA 6X, 30X, HAMAMELIS VIRGINIANA 12X, HYPERICUM PERFORATUM 12X, RHUS TOXICODENDRON 12X, RUTA GRAVEOLENS 12X, VERATRUM ALBUM 12X

INDICATIONS:

For temporary relief of soreness. Pain and swelling in joints.

WARNINGS:

Keep out of reach of children. In case of overdose, get medical help or contact a Poison Control Center right away.

If pregnant or breast-feeding, ask a health professional before use.

Do not use if tamper evident seal is broken or missing.

Keep out of reach of children. In case of overdose, get medical help or contact a Poison Control Center right away.

DIRECTIONS:

10 drops orally, 3 times a day. Consult a physician for use in children under 12 years of age.

INDICATIONS:

For temporary relief of soreness. Pain and swelling in joints.

INACTIVE INGREDIENTS:

Demineralized Water, 25% Ethanol

QUESTIONS:

Distributed by:

SYNERGY FORMULAS, INC.

251 West Road

Campobello, SC 29322

PACKAGE DISPLAY LABEL:

Synergy Formulas

INJURY COMPOSITION

HOMEOPATHIC

2 FL OZ (60 ml)